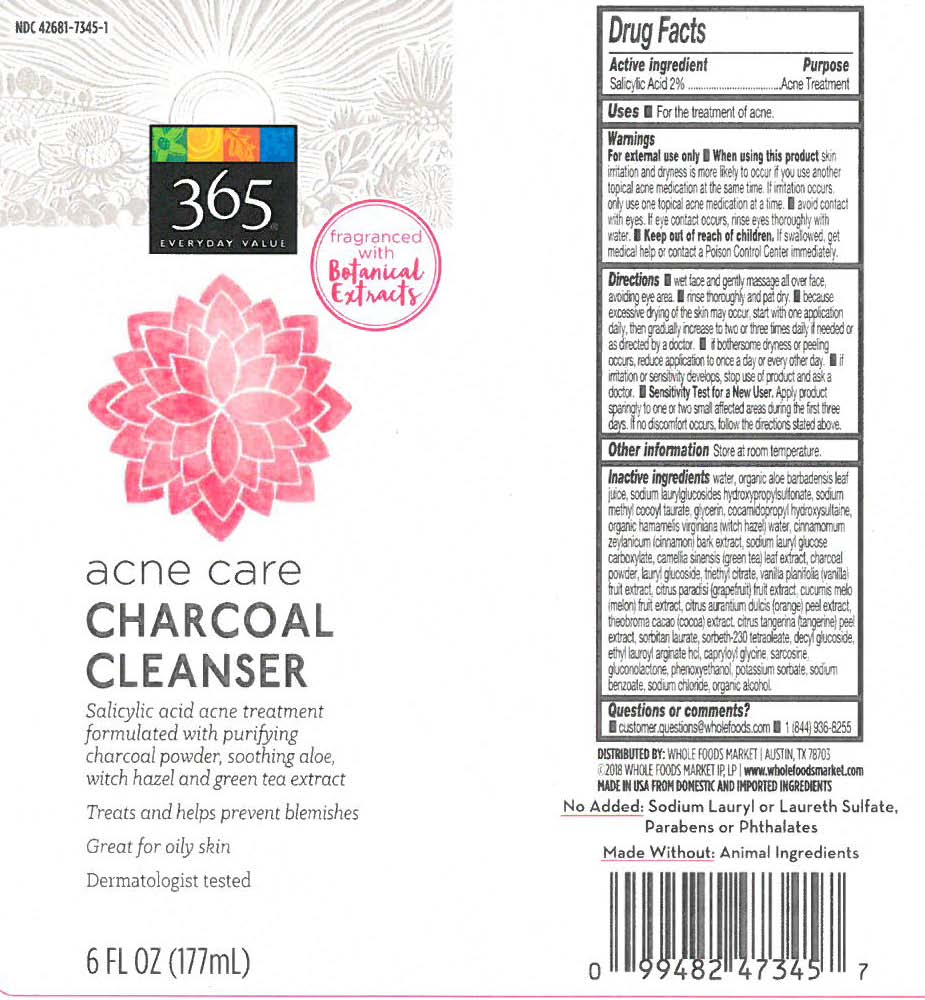 DRUG LABEL: Acne Care Charcoal Cleanser
NDC: 42681-7345 | Form: LIQUID
Manufacturer: Whole Foods Market
Category: otc | Type: HUMAN OTC DRUG LABEL
Date: 20251230

ACTIVE INGREDIENTS: SALICYLIC ACID 3.61 g/3.61 g
INACTIVE INGREDIENTS: WATER

Acne Care Charcoal Cleanser

Drug Facts

Active Ingrediets______________Purpose

Salicylic Acid 2%______________Acne Treatment

PURPOSE

Salicylic Acid 2%_________Acne Treatment

When using this product skin irritation and dryness is more likely to occur if you use another topical acne medication at the same time. avoid contact with eyes. If eye contact occurs, rinse eyes thoroughly with water. Keep out of reach of children. If swallowed, get medical help or contact a Poison control Center immediately.

Other Information Store at room temperature.

Directions

- wet face and gently massage all over face, avoiding eye area
- rinse thoroughly and pat dry
- because excessive drying of the skin may occur, start with one application daily, then gradually increase to two or three times daily if needed or as directed by doctor
- if bothersome dryness or peeling occurs, reduce application to once a day or every other day
- if irritation or sensitivity develops, stop use of product and ask a doctor
- Sensitivity Test for a New User: Apply product sparingly to one or two small affected areas during the first 3 days. If no discomfort occurs, follow the directions stated above.

INACTIVE INGREDIENT

Inactive Ingredients Water, Organic Aloe Barbadensis Leaf Juice, Sodium Laurylglucosides Hydroxypropylsulfonate, Sodium Methyl Cocoyl Taurate, Glycerin, Cocamidopropyl Hydroxysultaine, Organic Hamamelis Virginiana (Witch Hazel) Water, Cinnamomum Zeylanicum (Cinnamon) Bark Extract, Sodium Lauryl Glucose Carboxylate, Camellia Sinensis (Green Tea) Leaf Extract, Charcoal Powder, Lauryl Glucoside, Triethyl Citrate, Vanilla Planifolia (Vanilla) Fruit Extract, Citrus Paradisi (Grapefruit) Fruit Extract, Cucumis Melo (Melon) Fruit Extract, Citrus Aurantium Dulcis (Orange) Peel Extract, Theobroma Cacao (Cocoa) Extract, Citrus Tangerina (Tangerine) Peel Extract, Sorbitan Laurate, Sorbeth‐230 Tetraoleate, Decyl Glucoside, Ethyl Lauroyl Arginate HCl, Capryloyl Glycine, Sarcosine, Gluconolactone, Phenoxyethanol, Potassium Sorbate, Sodium Benzoate, Sodium Chloride, Organic Alcohol.

Questions or Comments?

customer.questions@wholefoods.com 1(844)936-8255

Warnings

For external use only

When using this product skin irritation and dryness is likely to occur if you use another topical acne medication at the same time. If irritation occurs, only use one topical acne medication at a time.

Avoid Contact with eyes. If eye contact occurs, rinse eyes thoroughly with water.

Keep out of reach of children. If swallowed, get medical help or contact a Poison Control Center immediately.

Directions

Wet face and gently massage all over face, avoiding eye area.

Rinse thoroughly and pat dry

Because excessive drying of the skin may occur, start with one application daily, then gradually increase to two or three times daily if needed or directed by a doctor.

If bothersome dryness or peeling occurs, reduce application to once a day or every other day.

If irritation or sensitivity develops, stop use of product and ask a doctor.

Sensitivity test for a New User. Apply product sparingly to one or two small affected areas during the first three days. If no discomfort occurs, follow the directions stated above.

Keep out of Reach of Children. If swallowed, get medical help or contact a Poison Control Center immediately.